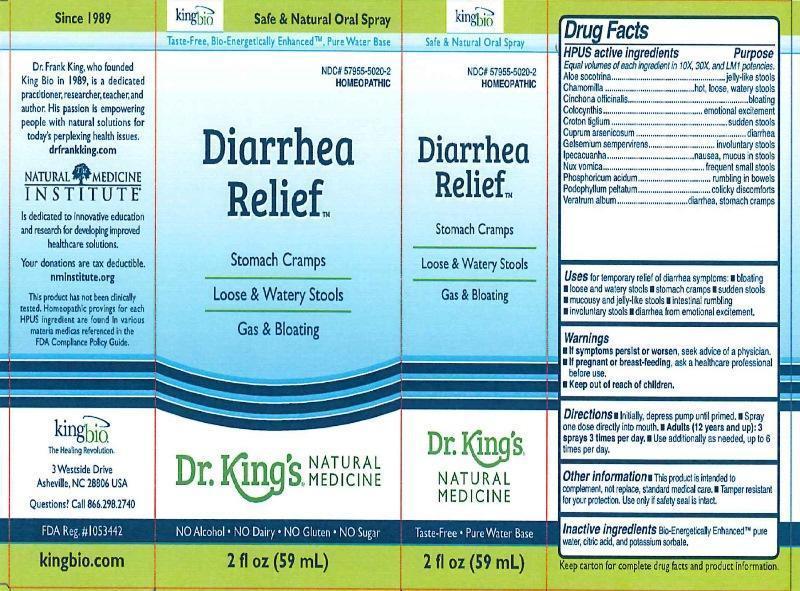 DRUG LABEL: Diarrhea Relief
NDC: 57955-5020 | Form: LIQUID
Manufacturer: King Bio Inc.
Category: homeopathic | Type: HUMAN OTC DRUG LABEL
Date: 20160317

ACTIVE INGREDIENTS: ALOE 10 [hp_X]/59 mL; MATRICARIA RECUTITA 10 [hp_X]/59 mL; CINCHONA OFFICINALIS BARK 10 [hp_X]/59 mL; CITRULLUS COLOCYNTHIS FRUIT PULP 10 [hp_X]/59 mL; CROTON TIGLIUM SEED 10 [hp_X]/59 mL; CUPRIC ARSENITE 10 [hp_X]/59 mL; GELSEMIUM SEMPERVIRENS ROOT 10 [hp_X]/59 mL; IPECAC 10 [hp_X]/59 mL; STRYCHNOS NUX-VOMICA SEED 10 [hp_X]/59 mL; PHOSPHORIC ACID 10 [hp_X]/59 mL; PODOPHYLLUM 10 [hp_X]/59 mL; VERATRUM ALBUM ROOT 10 [hp_X]/59 mL
INACTIVE INGREDIENTS: WATER; ANHYDROUS CITRIC ACID; POTASSIUM SORBATE

Diarrhea Relief™

ACTIVE INGREDIENT

Drug Facts__________________________________________________________________________________________________________

HPUS active ingredients: Aloe socotrina, Chamomilla, Cinchona officinalis, Colocynthis, Croton tiglium, Cuprum arsenicosum, Gelsemium sempervirens, Ipecacuanha, Nux vomica, Phosphoricum acidum, Podophyllum peltatum, Veratrum album. Equal volumes of each ingredient in 10X, 30X, and LM1 potencies.

INDICATIONS AND USAGE

Uses for temporary relief of diarrhea symptoms: •bloating •loose and watery stools •stomach cramps •sudden stools •mucousy and jelly-like stools •intestinal rumbling •involuntary stools •diarrhea from emotional excitement

Warnings

- If symptoms persist or worsen, seek advice of a physician.
- If pregnant or breast-feeding, ask a healthcare professional before use.

- Keep out of reach of children.

Directions

- Initially, depress pump until primed.
- Spray one dose directly into mouth.
- Adults (12 and up): 3 sprays 3 times per day.
- Use addittionlly as needed, up to 6 times per day.

Other information: •This product is intended to complement, not replace, standard medical care. •Tamper resistant for your protection. •Use only if safety seal is intact. •Keep carton for addional drug facts and product information.

Inactive Ingredients:

Bio-Energetically Enhanced™ pure water, citric acid and potassium sorbate.

Drug Facts

____________________________________________________________________________________________________________

HPUS active ingredients Purpose

Equal volumes of each ingredient in 10X, 30X, and LM1 potencies.

Aloe socotrina....................................................jelly-like stools

Chamomilla..........................................hot, loose, watery stools

Cinchona officinalis......................................................bloating

Colocynthis...............................................emotional excitement

Croton tiglium....................................................sudden stools

Cuprum arsenicosum..................................................diarrhea

Gelsemium sempervirens...............................involuntary stools

Ipecacuanha......................................nausea, mucus in stoools

Nux vomica.............................................frequent small stools

Phosphoricum acidum.................................rumbling in bowels

Podophyllum peltatum.................................colicky discomforts

Veratrum album...............................diarrhea, stomach cramps